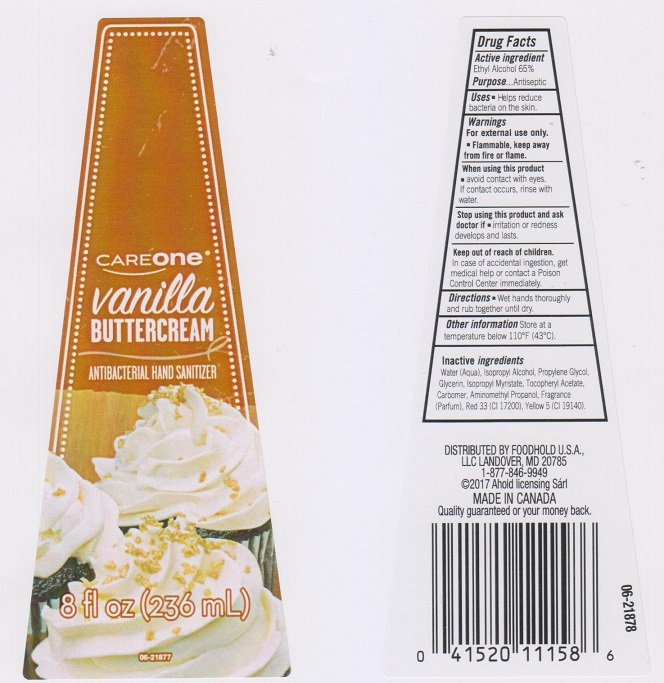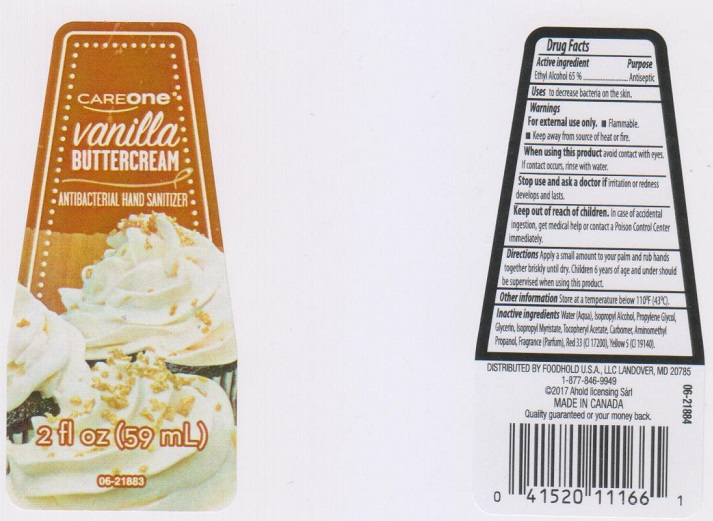 DRUG LABEL: Careone Vanilla Buttercream Hand Sanitizer
NDC: 41520-058 | Form: LIQUID
Manufacturer: American Sales Company
Category: otc | Type: HUMAN OTC DRUG LABEL
Date: 20170926

ACTIVE INGREDIENTS: ALCOHOL 650 mg/1 mL
INACTIVE INGREDIENTS: WATER; ISOPROPYL ALCOHOL; PROPYLENE GLYCOL; GLYCERIN; ISOPROPYL MYRISTATE; .ALPHA.-TOCOPHEROL ACETATE, DL-; CARBOMER 934; AMINOMETHYLPROPANOL; D&C RED NO. 33; FD&C YELLOW NO. 5

Drug Facts

Active ingredient

Ethyl Alcohol 65%

Purpose

Antiseptic

Uses

- helps reduce bacteria on the skin

Warnings

For external use only

- flammable, keep away from source of heat or fire

When using this product

- avoid contact with eyes. If contact occurs, rinse eyes thoroughly with water.

Stop using this product and ask a doctor if

- irritation or redness develops and lasts.

Keep out of reach of children.

In case of accidental ingestion, get medical help or contact a Poison Control Center immediately.

Directions

- wet hands thoroughly and rub together until dry.

Other information

store at a temperature below 110°F (43°C)

Inactive ingredients

Water (Aqua), Isopropyl Alcohol, Propylene Glycol, Glycerin, Isopropyl Myristate, Tocopheryl Acetate, Carbomer, Aminomethyl Propanol, Fragrance (Parfum), Red 33 (CI 17200), Yellow 5 (CI 19140).